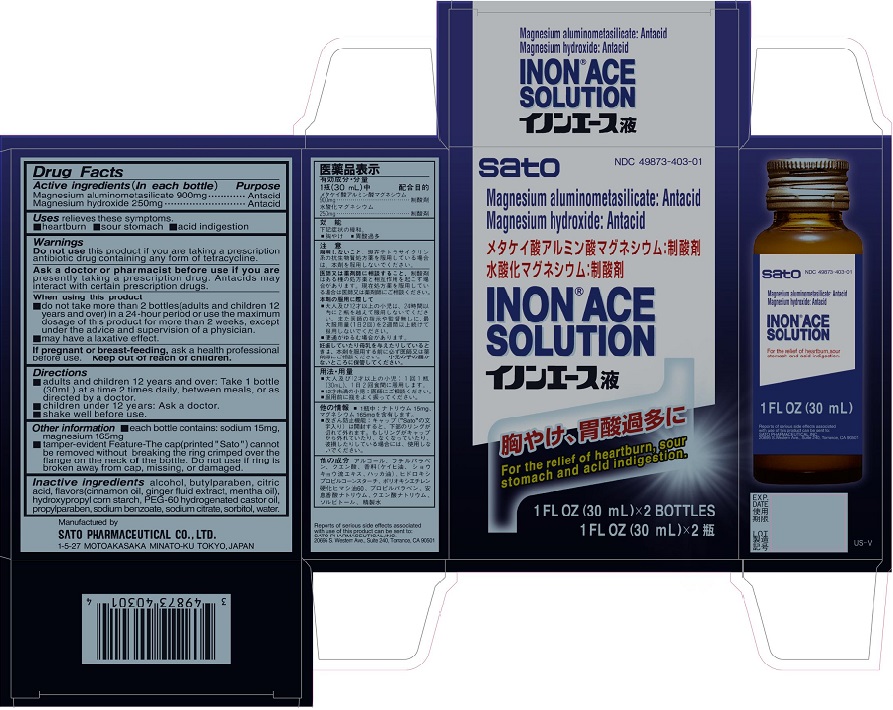 DRUG LABEL: Inon Ace
NDC: 49873-403 | Form: SOLUTION
Manufacturer: Sato Pharmaceutical Co., Ltd.
Category: otc | Type: HUMAN OTC DRUG LABEL
Date: 20231206

ACTIVE INGREDIENTS: SILODRATE 900 mg/30 mL; MAGNESIUM HYDROXIDE 250 mg/30 mL
INACTIVE INGREDIENTS: ALCOHOL; BUTYLPARABEN; CITRIC ACID MONOHYDRATE; HYDROXYPROPYL CORN STARCH (5% SUBSTITUTION BY WEIGHT); POLYOXYL 60 HYDROGENATED CASTOR OIL; PROPYLPARABEN; SODIUM BENZOATE; SODIUM CITRATE; SORBITOL; WATER

Inon Ace Solution

Active ingredients (in each bottle)
Magnesium Aluminosilicate 900 mg
Magnesium Hydroxide 250 mg

Purpose
Magnesium Aluminosilicate Antacid
Magnesium Hydroxide Antacid

INDICATIONS AND USAGE

Uses relieves these symptoms:
■ heartburn ■ sour stomach ■ acid indigestion

Warnings

Do not use this product if you are taking a prescription antibiotic drug containing any
form of tetracycline.

Ask a doctor or pharmacist before use if you are presently taking a prescription drug.
Antacids may interact with certain prescription drugs.

When using this product
■ do not take more than 2 bottles (adults and children 12 years and over) in a 24-hour
period or use the maximum dosage of this product for more than 2 weeks, except under
the advice and supervision of a physician.
■ may have a laxative effect.

PREGNANCY OR BREAST FEEDING

If pregnant or breast-feeding, ask a health professional before use.

Keep out of reach of children.

Directions
■ adults and children 12 years and over: Take 1 bottle (30mL) at a time 2 times daily,
between meals, or as directed by a doctor.
■ children under 12 years: Ask a doctor.
■ shake well before use.

Other information
■ each bottle contains: sodium 15 mg, magnesium 165 mg

INACTIVE INGREDIENT

Inactive ingredients alcohol, butylparaben, citric acid, flavors (cinnamon oil, fluid
extract of ginger root, spearmint oil), hydroxypropylstarch, PEG-60 hydrogenated castor
oil, propylparaben, sodium benzoate, sodium citrate, sorbitol, water.